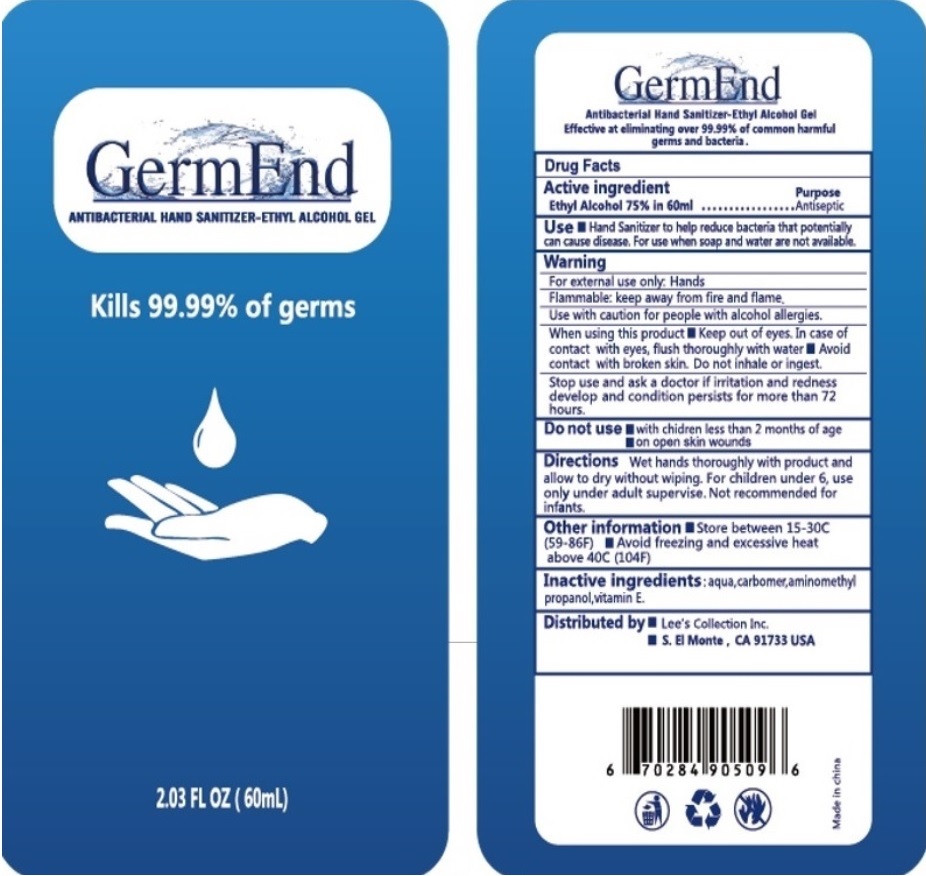 DRUG LABEL: GermEnd
NDC: 74027-300 | Form: GEL
Manufacturer: Lee's Collection Inc.
Category: otc | Type: HUMAN OTC DRUG LABEL
Date: 20200804

ACTIVE INGREDIENTS: ALCOHOL 75 mL/100 mL
INACTIVE INGREDIENTS: WATER; CARBOMER HOMOPOLYMER, UNSPECIFIED TYPE; AMINOMETHYLPROPANOL; .ALPHA.-TOCOPHEROL

GermEnd ANTIBACTERIAL HAND SANITIZER-ETHYL ALCOHOL GEL

Active ingredient

Ethyl Alcohol 75% in 60ml

Purpose

Antiseptic

INDICATIONS AND USAGE

Use • Hand Sanitizer to help reduce bacteria that potentially can cause disease. For use when soap and water are not available.

Warning

For external use only: Hands

Flammable: keep away from fire and flame.

Use with caution for people with alcohol allergies.

When using this product • Keep out of eyes. In case of contact with eyes, flush thoroughly with water • Avoid contact with broken skin. Do not inhale or ingest.

Stop use and ask a doctor if irritation and redness develop and condition persists for more than 72 hours.

Do not use • with children less than 2 months of age

• on open skin wounds

Keep out of reach of children. If swallowed, get medical help or contact Poison Control Center right away.

DOSAGE AND ADMINISTRATION

Directions Wet hands thoroughly with product and allow to dry without wiping. For children under 6, use only under adult supervise. Not recommended for infants.

Other information • Store between 15-30C (59-86F) • Avoid freezing and excessive heat above 40C (104F)

Inactive ingredients : aqua,carbomer,aminomethyl propanol,vitamin E.

Kills 99.99% of germs

Effective at eliminating over 99.99% of common harmful germs and bacteria.

Distributed by • Lee's Collection Inc.

• S. El Monte , CA 91733 USA

Made in China